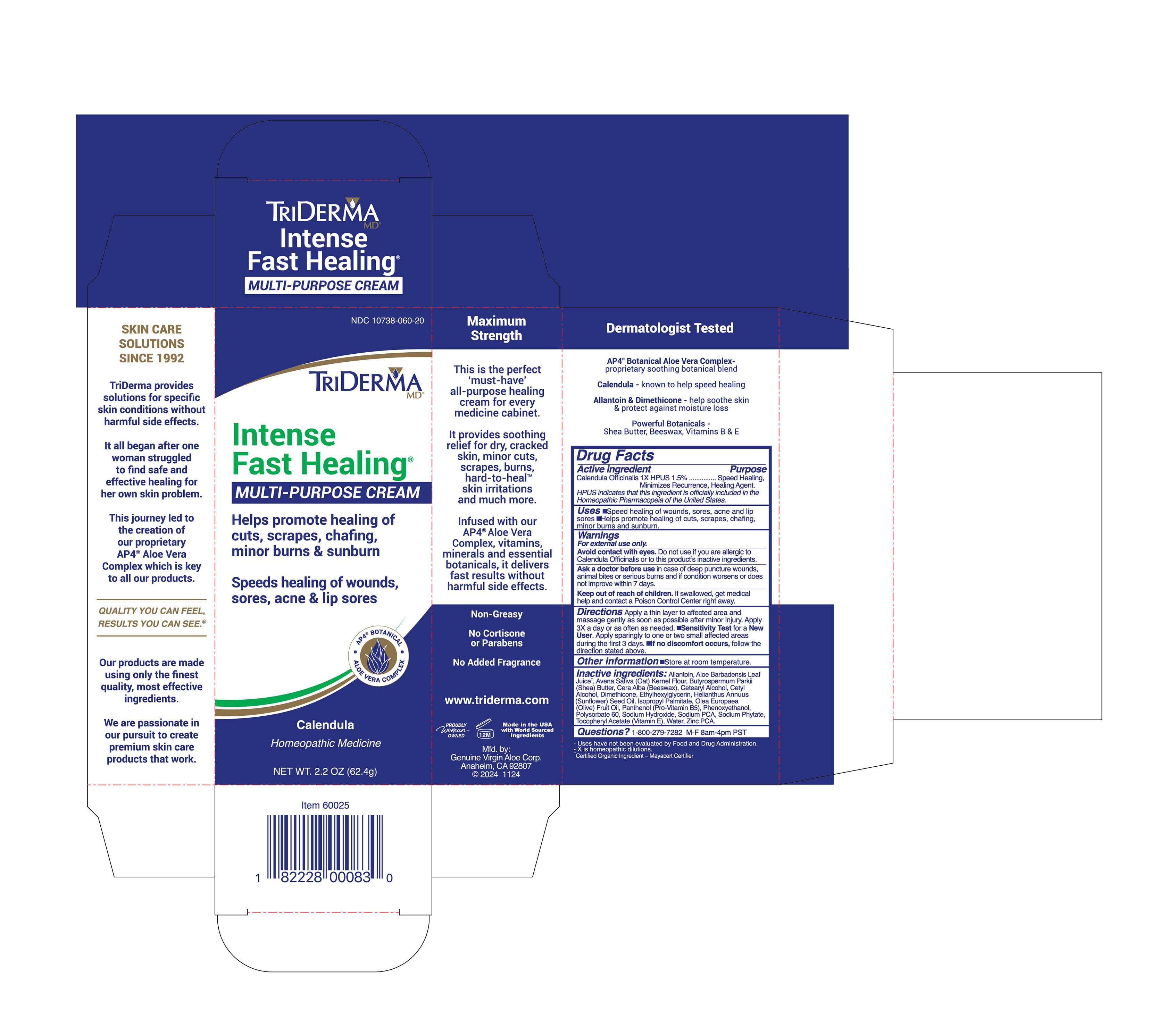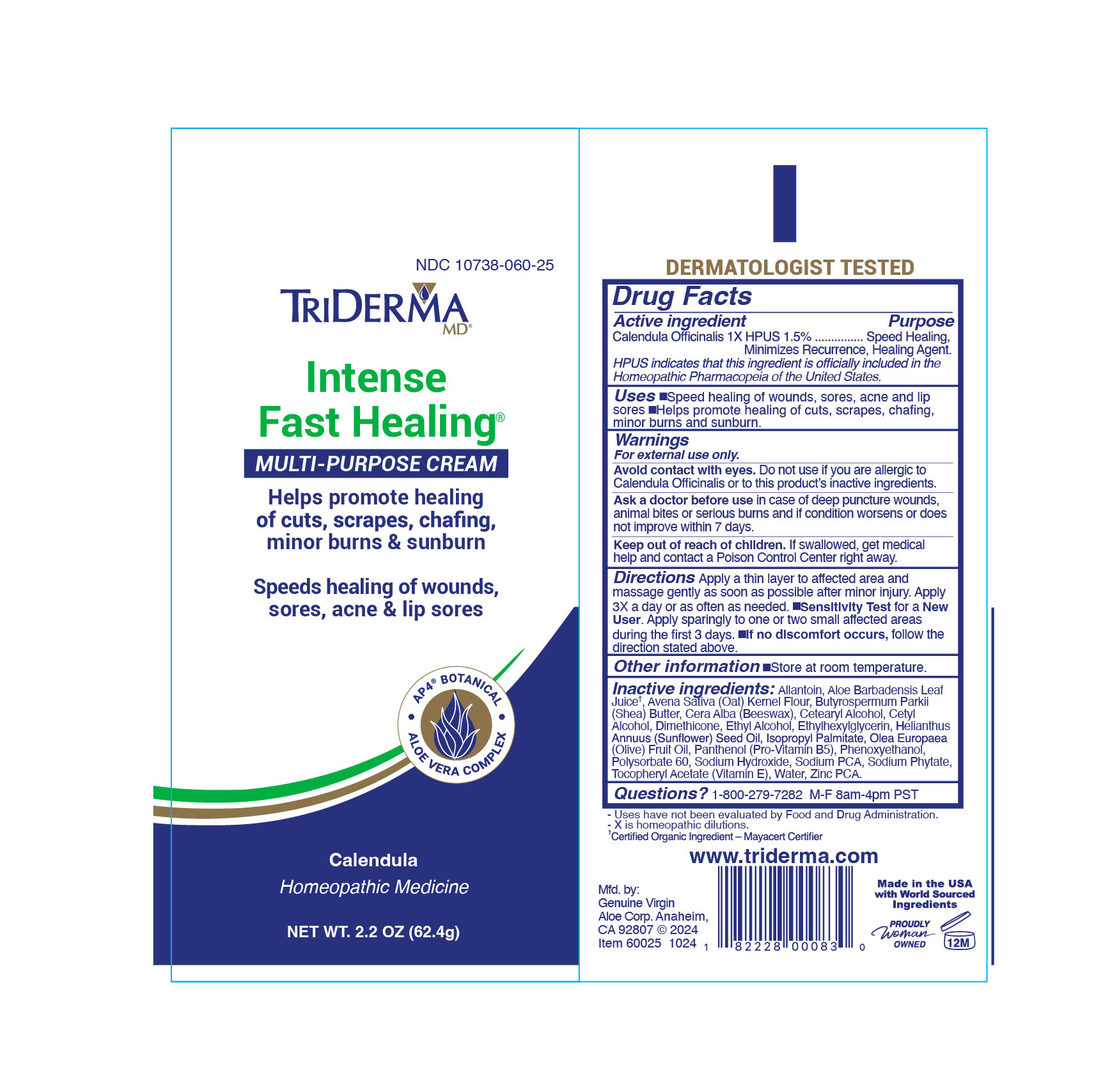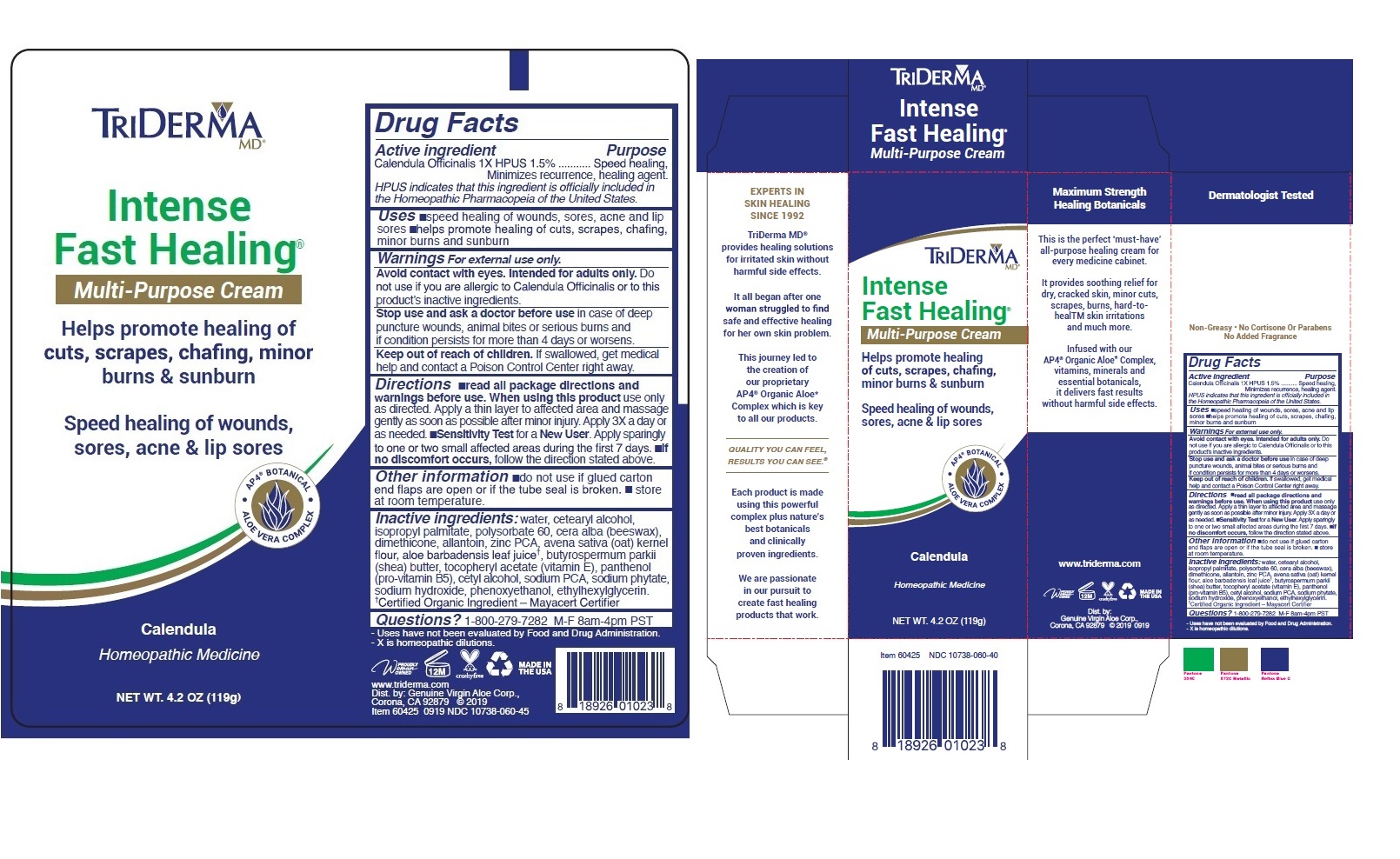 DRUG LABEL: TRIDERMA Intense Fast Healing Multi-Purpose Cream
NDC: 10738-060 | Form: CREAM
Manufacturer: Genuine Virgin Aloe Corporation
Category: homeopathic | Type: HUMAN OTC DRUG LABEL
Date: 20260128

ACTIVE INGREDIENTS: CALENDULA OFFICINALIS FLOWER 1.5 g/100 g
INACTIVE INGREDIENTS: WATER; CETOSTEARYL ALCOHOL; ISOPROPYL PALMITATE; POLYSORBATE 60; WHITE WAX; DIMETHICONE; ALLANTOIN; ZINC PCA; OATMEAL; ALOE VERA LEAF; SHEA BUTTER; .ALPHA.-TOCOPHEROL ACETATE; PANTHENOL; CETYL ALCOHOL; SODIUM PYRROLIDONE CARBOXYLATE; PHYTATE SODIUM; SODIUM HYDROXIDE; PHENOXYETHANOL; ETHYLHEXYLGLYCERIN

TRIDERMA Intense Fast Healing® Multi-Purpose Cream

Active ingredient

Calendula Officinalis 1x HPUS 1.5%

Purpose

Speed healing, Minimizes recurrence, healing agent.

HPUS indicates that this ingredient is officially included in the Homeopathic Pharmacopeia of the United States.

INDICATIONS AND USAGE

Uses •speed healing of wounds, sores, acne and lip sores •helps promote healing of cuts, scrapes, chafing, minor burns and sunburn

Warnings For external use only.

Avoid contact with eyes. Intended for adults only. Do not use if you allergic to Calendula Officinalis or to this product's inactive ingredients.

Stop use and ask a doctor before use in case of deep puncture wounds, animal bites or serious burns and if condition persists for more than 4 days or worsens.

Keep out of reach of children. If swallowed, get medical help and contact a Poison Control Center right away.

DOSAGE AND ADMINISTRATION

Directions •read all package directions and warnings before use. When using this product use only as directed. Apply a thin layer to affected area and massage gently as soon as possible after minor injury. Apply 3X a day or as needed. • Sensitivity Test for a New User. Apply sparingly to one or two small affected areas during the first 7 days. • if no discomfort occurs, follow the direction stated above.

Other information •do not use if glued carton end flaps are open or if the tube seal is broken. •store at room temperature.

INACTIVE INGREDIENT

Inactive ingredients: water, cetearyl alcohol, isopropyl palmitate, polysorbate 60, cera alba (beeswax), dimethicone, allantoin, zinc PCA, avena sativa (oat) kernel flour, aloe barbadensis leaf juice †, butyrospermum parkii (shea) butter, tocopheryl acetate (vitamin E), panthenol (pro-vitamin B5), cetyl alcohol, sodium PCA, sodium phytate, sodium hydroxide, phenoxyethanol, ethylhexylglycerin.

†Certified Organic Ingredient -Mayacert Certifier

QUESTIONS

Questions? 1-800-279-7282 M-F 8am-4pm PST

Helps promote healing of cuts, scrapes, chafing, minor burns & sunburn

Speed healing of wounds, sores, acne & lip sores

AP 4 ® BOTANICAL

ALOE VERA COMPLEX

Homeopathic Medicine

Maximum Strength Healing Botanicals

This is the perfect ‘must-have’ all-purpose healing cream for every medicine cabinet.

It provides soothing relief for dry, cracked skin, minor cuts, scrapes, burns, hard-tohealTM skin irritations and much more.

Infused with our AP4 ® Organic Aloe* Complex, vitamins, minerals and essential botanicals, it delivers fast results without harmful side effects.

EXPERTS IN SKIN HEALING SINCE 1992

TriDerma MD ® provides healing solutions for irritated skin without harmful side effects.

It all began after one women struggled to find safe and effective healing for her own skin problem.

This journey led to the creation of our proprietary AP4 ® Organic Aloe* Complex which is key to all our products .

QUALITY YOU CAN FEEL, RESULTS YOU CAN SEE ®

Each product is made using this powerful complex plus nature’s best botanicals and clinically proven ingredients.

We are passionate in our pursuit to create fast healing products that work.

Non-Greasy • No Cortisone Or Parabens

No Added Fragrance

- Uses have not been evaluated by Food and Drug Administration.

- X is homeopathic dilutions.

MADE IN THE USA

www.triderma.com

Dist. by: Genuine Virgin Aloe Corp, Corona, CA 92879 © 2019

Item 60425 0919